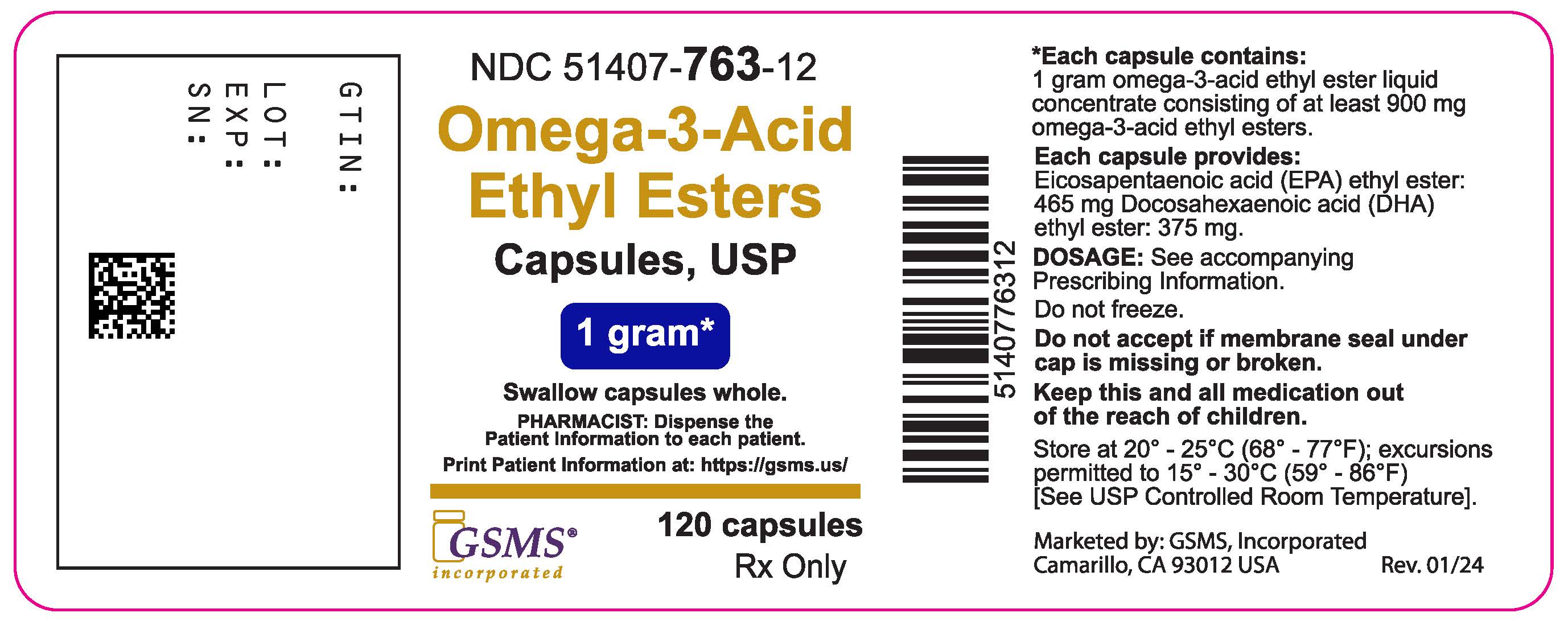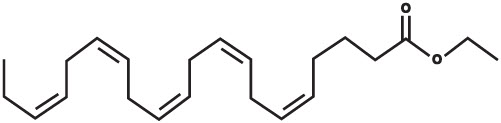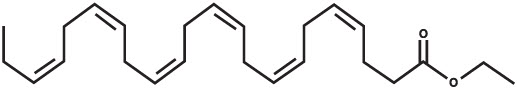 DRUG LABEL: Omega-3-Acid Ethyl Esters
NDC: 51407-763 | Form: CAPSULE
Manufacturer: Golden State Medical Supply, Inc.
Category: prescription | Type: HUMAN PRESCRIPTION DRUG LABEL
Date: 20250224

ACTIVE INGREDIENTS: OMEGA-3-ACID ETHYL ESTERS 1 g/1 1
INACTIVE INGREDIENTS: .ALPHA.-TOCOPHEROL; GELATIN, UNSPECIFIED; GLYCERIN; WATER

HIGHLIGHTS OF PRESCRIBING INFORMATION

OMEGA-3-ACID ETHYL ESTERS CAPSULES. These highlights do not include all the information needed to use OMEGA-3-ACID ETHYL ESTERS CAPSULES safely and effectively. See full prescribing information for OMEGA-3-ACID ETHYL ESTERS CAPSULES.
OMEGA-3-ACID ETHYL ESTERS capsules, for oral use
Initial U.S. Approval: 2004

1 INDICATIONS AND USAGE

Omega-3-acid ethyl esters capsules are a combination of ethyl esters of omega 3 fatty acids, principally eicosapentaenoic acid (EPA) and docosahexaenoic acid (DHA), indicated as an adjunct to diet to reduce triglyceride (TG) levels in adult patients with severe (≥500 mg/dL) hypertriglyceridemia (HTG). (1)

Limitations of Use:

- The effect of omega-3-acid ethyl esters on the risk for pancreatitis has not been determined. (1)
- The effect of omega-3-acid ethyl esters on cardiovascular mortality and morbidity has not been determined. (1)

2 DOSAGE AND ADMINISTRATION

- The daily dose of omega-3-acid ethyl esters is 4 grams per day taken as a single 4-gram dose (4 capsules) or as two 2-gram doses (2 capsules given twice daily). (2)
- Patients should be advised to swallow omega-3-acid ethyl esters whole. Do not break open, crush, dissolve, or chew omega-3-acid ethyl esters. (2)

3 DOSAGE FORMS AND STRENGTHS

Capsules: 1 gram (3)

4 CONTRAINDICATIONS

Omega-3-acid ethyl esters are contraindicated in patients with known hypersensitivity (e.g., anaphylactic reaction) to omega-3-acid ethyl esters or any of its components. (4)

5 WARNINGS AND PRECAUTIONS

- In patients with hepatic impairment, monitor ALT and AST levels periodically during therapy. (5.1)
- Omega-3-acid ethyl esters may increase levels of LDL. Monitor LDL levels periodically during therapy. (5.1)
- Use with caution in patients with known hypersensitivity to fish and/or shellfish. (5.2)
- There is a possible association between omega-3-acid ethyl esters and more frequent recurrences of symptomatic atrial fibrillation or flutter in patients with paroxysmal or persistent atrial fibrillation, particularly within the first months of initiating therapy. (5.3)

6 ADVERSE REACTIONS

The most common adverse reactions (incidence >3% and greater than placebo) were eructation, dyspepsia, and taste perversion. (6)

To report SUSPECTED ADVERSE REACTIONS, contact KD Pharma USA at 1-877-241-7978 or FDA at 1-800-FDA-1088 or www.fda.gov/medwatch

7 DRUG INTERACTIONS

Omega-3-acids may prolong bleeding time. Patients taking omega-3-acid ethyl esters and an anticoagulant or other drug affecting coagulation (e.g., anti-platelet agents) should be monitored periodically. (7.1)

8 USE IN SPECIFIC POPULATIONS

- Pregnancy: Use during pregnancy only if the potential benefit justifies the potential risk to the fetus. (8.1)

FULL PRESCRIBING INFORMATION

1 INDICATIONS AND USAGE

Omega-3-acid ethyl esters capsules are indicated as an adjunct to diet to reduce triglyceride (TG) levels in adult patients with severe (greater than or equal to 500 mg per dL) hypertriglyceridemia (HTG).

Usage Considerations:Patients should be placed on an appropriate lipid-lowering diet before receiving omega-3-acid ethyl esters and should continue this diet during treatment with omega-3-acid ethyl esters.

Laboratory studies should be done to ascertain that the lipid levels are consistently abnormal before instituting therapy with omega-3-acid ethyl esters. Every attempt should be made to control serum lipids with appropriate diet, exercise, weight loss in obese patients, and control of any medical problems such as diabetes mellitus and hypothyroidism that are contributing to the lipid abnormalities. Medications known to exacerbate hypertriglyceridemia (such as beta blockers, thiazides, estrogens) should be discontinued or changed if possible prior to consideration of triglyceride-lowering drug therapy.

Limitations of Use:

The effect of omega-3-acid ethyl esters on the risk for pancreatitis has not been determined.

The effect of omega-3-acid ethyl esters on cardiovascular mortality and morbidity has not been determined.

2 DOSAGE AND ADMINISTRATION

- Assess triglyceride levels carefully before initiating therapy. Identify other causes (e.g., diabetes mellitus, hypothyroidism, medications) of high triglyceride levels and manage as appropriate [see Indications and Usage (1)].
- Patients should be placed on an appropriate lipid-lowering diet before receiving omega-3-acid ethyl esters, and should continue this diet during treatment with omega-3-acid ethyl esters. In clinical studies, omega-3-acid ethyl esters was administered with meals.

The daily dose of omega-3-acid ethyl esters is 4 grams per day. The daily dose may be taken as a single 4-gram dose (4 capsules) or as two 2-gram doses (2 capsules given twice daily).

Patients should be advised to swallow omega-3-acid ethyl esters whole. Do not break open, crush, dissolve, or chew omega-3-acid ethyl esters.

3 DOSAGE FORMS AND STRENGTHS

Omega-3-acid ethyl esters capsules USP are supplied as 1-gram oblong, clear, soft gel capsules filled with slightly yellow to yellow liquid and imprinted with "GLW" in white ink across one side.

4 CONTRAINDICATIONS

Omega-3-acid ethyl esters are contraindicated in patients with known hypersensitivity (e.g., anaphylactic reaction) to omega-3-acid ethyl esters or any of its components.

5 WARNINGS AND PRECAUTIONS

5.1 Monitoring: Laboratory Tests

In patients with hepatic impairment, alanine aminotransferase (ALT) and aspartate aminotransferase (AST) levels should be monitored periodically during therapy with omega-3-acid ethyl esters. In some patients, increases in ALT levels without a concurrent increase in AST levels were observed.

In some patients, omega-3-acid ethyl esters increases LDL-C levels. LDL-C levels should be monitored periodically during therapy with omega-3-acid ethyl esters.

Laboratory studies should be performed periodically to measure the patient's TG levels during therapy with omega-3-acid ethyl esters.

5.2 Fish Allergy

Omega-3-acid ethyl esters contain ethyl esters of omega-3 fatty acids (EPA and DHA) obtained from the oil of several fish sources. It is not known whether patients with allergies to fish and/or shellfish, are at increased risk of an allergic reaction to omega-3-acid ethyl esters. Omega-3-acid ethyl esters should be used with caution in patients with known hypersensitivity to fish and/or shellfish.

5.3 Recurrent Atrial Fibrillation (AF) or Flutter

In a double-blind, placebo-controlled trial of 663 subjects with symptomatic paroxysmal AF (n = 542) or persistent AF (n = 121), recurrent AF or flutter was observed in subjects randomized to omega-3-acid ethyl esters who received 8 grams per day for 7 days and 4 grams per day thereafter for 23 weeks at a higher rate relative to placebo. Subjects in this trial had median baseline triglycerides of 127 mg per dL, had no substantial structural heart disease, were taking no anti-arrhythmic therapy (rate control permitted), and were in normal sinus rhythm at baseline.

At 24 weeks, in the paroxysmal AF stratum, there were 129 (47%) first recurrent symptomatic AF or flutter events on placebo and 141 (53%) on omega-3-acid ethyl esters [primary endpoint, HR 1.19; 95% CI: 0.93, 1.35]. In the persistent AF stratum, there were 19 (35%) events on placebo and 34 (52%) events on omega-3-acid ethyl esters [HR 1.63; 95% CI: 0.91, 2.18]. For both strata combined, the HR was 1.25; 95% CI: 1.00, 1.40. Although the clinical significance of these results is uncertain, there is a possible association between omega-3-acid ethyl esters and more frequent recurrences of symptomatic atrial fibrillation or flutter in patients with paroxysmal or persistent atrial fibrillation, particularly within the first 2 or 3 months of initiating therapy.

Omega-3-acid ethyl esters are not indicated for the treatment of AF or flutter.

6 ADVERSE REACTIONS

6.1 Clinical Trials Experience

Because clinical trials are conducted under widely varying conditions, adverse reaction rates observed in the clinical trials of a drug cannot be directly compared with rates in the clinical trials of another drug and may not reflect the rates observed in practice.

Adverse reactions reported in at least 3% of subjects treated with Omega-3-acid ethyl esters and at with omega-3-acid ethyl esters based on pooled data across 23 clinical trials are listed in Table 1.

Adverse Reaction [Trials included subjects with HTG and severe HTG.] | Omega-3-acid ethyl esters (n = 655) |  | Placebo (n = 370)
 | n | % | n | %
Eructation | 29 | 4 | 5 | 1
Dyspepsia | 22 | 3 | 6 | 2
Taste perversion | 27 | 4 | 1 | <1

Additional adverse reactions from clinical trials are listed below:

Digestive System

Constipation, gastrointestinal disorder and vomiting.

Metabolic and Nutritional Disorders

Increased ALT and increased AST.

Skin

Pruritus and rash.

6.2 Postmarketing Experience

In addition to adverse reactions reported from clinical trials, the events described below have been identified during post-approval use of omega-3-acid ethyl esters. Because these events are reported voluntarily from a population of unknown size, it is not possible to reliably estimate their frequency or to always establish a causal relationship to drug exposure.

The following events have been reported: anaphylactic reaction, hemorrhagic diathesis, urticaria.

7 DRUG INTERACTIONS

7.1 Anticoagulants or Other Drugs Affecting Coagulation

Some trials with omega-3-acids demonstrated prolongation of bleeding time. The prolongation of bleeding time reported in these trials has not exceeded normal limits and did not produce clinically significant bleeding episodes. Clinical trials have not been done to thoroughly examine the effect of omega-3-acid ethyl esters and concomitant anticoagulants. Patients receiving treatment with omega-3-acid ethyl esters and an anticoagulant or other drug affecting coagulation (e.g., anti-platelet agents) should be monitored periodically.

8 USE IN SPECIFIC POPULATIONS

8.1 Pregnancy

Pregnancy Category C: There are no adequate and well-controlled studies in pregnant women. It is unknown whether omega-3-acid ethyl esters can cause fetal harm when administered to a pregnant woman or can affect reproductive capacity.Omega-3-acid ethyl esters should be used during pregnancy only if the potential benefit to the patient justifies the potential risk to the fetus.

Animal Data

Omega-3-acid ethyl esters have been shown to have an embryocidal effect in pregnant rats when given in doses resulting in exposures 7 times the recommended human dose of 4 grams per day based on a body surface area comparison.

In female rats given oral gavage doses of 100, 600, and 2,000 mg per kg per day beginning 2 weeks prior to mating and continuing through gestation and lactation, no adverse effects were observed in the high-dose group (5 times human systemic exposure following an oral dose of 4 grams per day based on body surface area comparison).

In pregnant rats given oral gavage doses of 1,000, 3,000, and 6,000 mg per kg per day from gestation Day 6 through 15, no adverse effects were observed (14 times human systemic exposure following an oral dose of 4 grams per day based on a body surface area comparison).

In pregnant rats given oral gavage doses of 100, 600, and 2,000 mg per kg per day from gestation Day 14 through lactation Day 21, no adverse effects were seen at 2,000 mg per kg per day (5 times the human systemic exposure following an oral dose of 4 grams per day based on a body surface area comparison). However, decreased live births (20% reduction) and decreased survival to postnatal Day 4 (40% reduction) were observed in a dose-ranging study using higher doses of 3,000 mg per kg per day (7 times the human systemic exposure following an oral dose of 4 grams per day based on a body surface area comparison).

In pregnant rabbits given oral gavage doses of 375, 750, and 1,500 mg per kg per day from gestation Day 7 through 19, no findings were observed in the fetuses in groups given 375 mg per kg per day (2 times human systemic exposure following an oral dose of 4 grams per day based on a body surface area comparison). However, at higher doses, evidence of maternal toxicity was observed (4 times human systemic exposure following an oral dose of 4 grams per day based on a body surface area comparison).

8.3 Nursing Mothers

Studies with omega-3-acid ethyl esters have demonstrated excretion in human milk. The effect of this excretion on the infant of a nursing mother is unknown; caution should be exercised when omega-3-acid ethyl esters are administered to a nursing mother. An animal study in lactating rats given oral gavage 14C-ethyl EPA demonstrated that drug levels were 6 to 14 times higher in milk than in plasma.

8.4 Pediatric Use

Safety and effectiveness in pediatric patients have not been established.

8.5 Geriatric Use

A limited number of subjects older than 65 years were enrolled in the clinical trials of omega-3-acid ethyl esters. Safety and efficacy findings in subjects older than 60 years did not appear to differ from those of subjects younger than 60 years.

9 DRUG ABUSE AND DEPENDENCE

Omega-3-acid ethyl esters do not have any known drug abuse or withdrawal effects.

11 DESCRIPTION

Omega-3-acid ethyl esters, USP, lipid-regulating agents, are supplied as a liquid-filled gel capsule for oral administration. Each 1-gram capsule of omega-3-acid ethyl esters, USP contains at least 900 mg of the ethyl esters of omega-3 fatty acids sourced from fish oils. These are predominantly a combination of ethyl esters of eicosapentaenoic acid (EP — approximately 465 mg) and docosahexaenoic acid (DHA — approximately 375 mg).

The empirical formula of EPA ethyl ester is C22H34O2, and the molecular weight of EPA ethyl ester is 330.51. The structural formula of EPA ethyl ester is:

The empirical formula of DHA ethyl ester is C24H36O2, and the molecular weight of DHA ethyl ester is 356.55. The structural formula of DHA ethyl ester is:

Omega-3-Acid Ethyl Esters Capsules USP also contain the following inactive ingredients: 4 mg alpha-tocopherol, gelatin, glycerin, hypromellose, propylene glycol, and titanium dioxide.

12 CLINICAL PHARMACOLOGY

12.1 Mechanism of Action

The mechanism of action of omega-3-acid ethyl esters is not completely understood. Potential mechanisms of action include inhibition of acyl-CoA:1,2-diacylglycerol acyltransferase, increased mitochondrial and peroxisomal β-oxidation in the liver, decreased lipogenesis in the liver, and increased plasma lipoprotein lipase activity. Omega-3-acid ethyl esters may reduce the synthesis of triglycerides in the liver because EPA and DHA are poor substrates for the enzymes responsible for TG synthesis, and EPA and DHA inhibit esterification of other fatty acids.

12.3 Pharmacokinetics

Absorption

In healthy volunteers and in subjects with hypertriglyceridemia, EPA and DHA were absorbed when administered as ethyl esters orally. Omega-3-acids administered as ethyl esters (omega-3-acid ethyl esters) induced significant dose-dependent increases in serum phospholipid EPA content, though increases in DHA content were less marked and not dose-dependent when administered as ethyl esters.

Special Populations

Age:Uptake of EPA and DHA into serum phospholipids in subjects treated with omega-3-acid ethyl esters was independent of age (younger than 49 years versus 49 years and older).

Male and Female Patients:Females tended to have more uptake of EPA into serum phospholipids than males. The clinical significance of this is unknown.

Pediatric Patients:Pharmacokinetics of omega-3-acid ethyl esters have not been studied.

Patients with Renal or Hepatic Impairment:Omega-3-acid ethyl esters has not been studied in patients with renal or hepatic impairment.

Drug Interaction Studies

Simvastatin:In a 14-day trial of 24 healthy adult subjects, daily coadministration of simvastatin 80 mg with omega-3-acid ethyl esters 4 grams did not affect the extent (AUC) or rate (Cmax) of exposure to simvastatin or the major active metabolite, beta-hydroxy simvastatin, at steady state.

Atorvastatin:In a 14-day trial of 50 healthy adult subjects, daily coadministration of atorvastatin 80 mg with omega-3-acid ethyl esters 4 grams did not affect AUC or Cmaxof exposure to atorvastatin, 2-hydroxyatorvastatin, or 4-hydroxyatorvastatin at steady state.

Rosuvastatin:In a 14-day trial of 48 healthy adult subjects, daily coadministration of rosuvastatin 40 mg with omega-3-acid ethyl esters 4 grams did not affect AUC or Cmaxof exposure to rosuvastatin at steady state.

In vitrostudies using human liver microsomes indicated that clinically significant cytochrome P450-mediated inhibition by EPA/DHA combinations are not expected in humans.

13 NONCLINICAL TOXICOLOGY

13.1 Carcinogenesis, Mutagenesis, Impairment of Fertility

In a rat carcinogenicity study with oral gavage doses of 100, 600, and 2,000 mg per kg per day, males were treated with omega-3-acid ethyl esters for 101 weeks and females for 89 weeks without an increased incidence of tumors (up to 5 times human systemic exposures following an oral dose of 4 grams per day based on a body surface area comparison). Standard lifetime carcinogenicity bioassays were not conducted in mice.

Omega-3-acid ethyl esters were not mutagenic or clastogenic with or without metabolic activation in the bacterial mutagenesis (Ames) test with Salmonella typhimuriumand Escherichia colior in the chromosomal aberration assay in Chinese hamster V79 lung cells or human lymphocytes. Omega-3-acid ethyl esters were negative in the in vivomouse micronucleus assay.

In a rat fertility study with oral gavage doses of 100, 600, and 2,000 mg per kg per day, males were treated for 10 weeks prior to mating and females were treated for 2 weeks prior to and throughout mating, gestation, and lactation. No adverse effect on fertility was observed at 2,000 mg per kg per day (5 times human systemic exposure following an oral dose of 4 grams per day based on a body surface area comparison).

14 CLINICAL STUDIES

14.1 Severe Hypertriglyceridemia

The effects of omega-3-acid ethyl esters 4 grams per day were assessed in 2 randomized, placebo-controlled, doubleblind, parallel-group trials of 84 adult subjects (42 on omega-3-acid ethyl esters, 42 on placebo) with very high triglyceride levels. Subjects whose baseline triglyceride levels were between 500 and 2,000 mg per dL were enrolled in these 2 trials of 6 and 16 weeks' duration. The median triglyceride and LDL-C levels in these subjects were 792 mg per dL and 100 mg per dL, respectively. Median high-density lipoprotein cholesterol (HDL-C) level was 23.0 mg per dL.

The changes in the major lipoprotein lipid parameters for the groups receiving omega-3-acid ethyl esters or placebo are shown in Table 2.

Table 2. Median Baseline and Percent Change from Baseline in Lipid Parameters in Subjects with Severe Hypertriglyceridemia (≥500 mg per dL)
Parameter | Omega-3-acid ethyl esters n=42 |  | Placebo n=42 |  | Difference
 | BL | % Change | BL | % Change
TG | 816 | -44.9 | 788 | +6.7 | -51.6
Non-HDL-C | 271 | -13.8 | 292 | -3.6 | -10.2
TC | 296 | -9.7 | 314 | -1.7 | -8.0
VLDL-C | 175 | -41.7 | 175 | -0.9 | -40.8
HDL-C | 22 | +9.1 | 24 | 0.0 | +9.1
LDL-C | 89 | +44.5 | 108 | -4.8 | +49.3
BL = Baseline (mg per dL); % Change = Median Percent Change from Baseline; Difference = Omega-3-acid ethyl esters Median % Change – Placebo Median % Change; VLDL-C = Very-low-density lipoprotein (VLDL) cholesterol.

Omega-3-acid ethyl esters 4 grams per day reduced median TG, VLDL-C, and non-HDL-C levels and increased median HDL-C from baseline relative to placebo. Treatment with omega-3-acid ethyl esters to reduce very high TG levels may result in elevations in LDL-C and non-HDL-C in some individuals. Patients should be monitored to ensure that the LDL-C level does not increase excessively.

The effect of omega-3-acid ethyl esters on the risk of pancreatitis has not been determined.

The effect of omega-3-acid ethyl esters on cardiovascular mortality and morbidity has not been determined.

16 HOW SUPPLIED/STORAGE AND HANDLING

Omega-3-Acid Ethyl Esters Capsules USP are available as follows: 1 gram – slightly yellow to yellow liquid, oblong, clear, soft gel capsules, imprinted with "GLW" in white ink across one side.

Bottles of 120: NDC 51407-763-12

STORAGE AND HANDLING

Store at 20°-25°C (68°-77°F); excursions permitted to 15° to 30°C (59° to 86°F) [see USP Controlled Room Temperature]. Do not freeze. Protect from light. Dispense in a tight, light-resistant container as defined in the USP, with a child-resistant closure (as required).

17 PATIENT COUNSELING INFORMATION

Advise the patient to read the FDA-approved patient labeling (Patient Information).

Information for Patients:

- Omega-3-acid ethyl esters should be used with caution in patients with known sensitivity or allergy to fish and/or shellfish [see Warnings and Precautions (5.2)] .
- Advise patients that use of lipid-regulating agents does not reduce the importance of adhering to diet [see Dosage and Administration (2)] .
- Advise patients not to alter omega-3-acid ethyl esters in any way and to ingest intact capsules only [see Dosage and Administration (2)] .
- Instruct patients to take omega-3-acid ethyl esters as prescribed. If a dose is missed, advise patients to take it as soon as they remember. However, if they miss one day of omega-3-acid ethyl esters, they should not double the dose when they take it.

Manufactured By:
Patheon Softgels Inc.
High Point, NC 27265
USA

Manufactured For:
KD Pharma USA Inc.
12021 SW 144th Street
Miami, Florida 33186
USA

Revised: November 2022

Marketed by:

GSMS, Inc.

Camarillo, CA 93012 USA

PATIENT INFORMATION

OMEGA-3-ACID ETHYL ESTERS CAPSULES, USP
(oh may' ga as' id eth' il es' ters).

What are OMEGA-3-ACID ETHYL ESTERS CAPSULES, USP?

OMEGA-3-ACID ETHYL ESTERS CAPSULES, USP are a prescription medicine used along with a low-fat and low-cholesterol diet to lower very high triglyceride (fat) levels in adults.

It is not known if OMEGA-3-ACID ETHYL ESTERS CAPSULES, USP change your risk of having inflammation of your pancreas (pancreatitis).

It is not known if OMEGA-3-ACID ETHYL ESTERS CAPSULES, USP prevent you from having a heart attack or stroke.

It is not known if OMEGA-3-ACID ETHYL ESTERS CAPSULES, USP are safe and effective in children.

Who should not take OMEGA-3-ACID ETHYL ESTERS CAPSULES, USP?

Do not take OMEGA-3-ACID ETHYL ESTERS CAPSULES, USP if you are allergic to omega-3-acid ethyl esters or any of the ingredients in OMEGA-3-ACID ETHYL ESTERS CAPSULES, USP. See the end of this leaflet for a complete list of ingredients in OMEGA-3-ACID ETHYL ESTERS CAPSULES, USP.

Before taking OMEGA-3-ACID ETHYL ESTERS CAPSULES, USP, tell your healthcare provider about all of your medical conditions, including if you:

- have diabetes.
- have a low thyroid problem (hypothyroidism).
- have a liver problem.
- have a pancreas problem.
- have a certain heart rhythm problem called atrial fibrillation or flutter.
- are allergic to fish or shellfish. It is not known if people who are allergic to fish or shellfish are also allergic to OMEGA-3-ACID ETHYL ESTERS CAPSULES, USP.
- are pregnant or plan to become pregnant. It is not known if OMEGA-3-ACID ETHYL ESTERS CAPSULES, USP will harm your unborn baby.
- are breastfeeding or plan to breastfeed. OMEGA-3-ACID ETHYL ESTERS CAPSULES, USP can pass into your breast milk. Talk to your healthcare provider about the best way to feed your baby if you take OMEGA-3-ACID ETHYL ESTERS CAPSULES, USP.

Tell your healthcare provider about all the medicines you take,including prescription and over-the-counter medicines, vitamins, and herbal supplements.

OMEGA-3-ACID ETHYL ESTERS CAPSULES, USP can interact with certain other medicines that you are taking. Using OMEGA-3-ACID ETHYL ESTERS CAPSULES, USP with medicines that affect blood clotting (anticoagulants or blood thinners) may cause serious side effects.

How should I take OMEGA-3-ACID ETHYL ESTERS CAPSULES, USP?

- Take OMEGA-3-ACID ETHYL ESTERS CAPSULES, USP exactly as your healthcare provider tells you to take them.
- You should not take more than 4 capsules of OMEGA-3-ACID ETHYL ESTERS CAPSULES, USP each day. Either take all 4 capsules at one time or 2 capsules two times a day.
- Do not change your dose or stop OMEGA-3-ACID ETHYL ESTERS CAPSULES, USP without talking to your healthcare provider.
- Take OMEGA-3-ACID ETHYL ESTERS CAPSULES, USP with food.
- Take OMEGA-3-ACID ETHYL ESTERS CAPSULES, USP whole. Do not break, open, crush, dissolve, or chew OMEGA-3-ACID ETHYL ESTERS CAPSULES, USP before swallowing. If you cannot swallow OMEGA-3-ACID ETHYL ESTERS CAPSULES, USP whole, tell your healthcare provider. You may need a different medicine.
- If you miss a dose of OMEGA-3-ACID ETHYL ESTERS CAPSULES, USP, take the missed dose as soon as you remember. If you miss one day of OMEGA-3-ACID ETHYL ESTERS CAPSULES, USP, do not double your dose the next time you take it.
- Your healthcare provider may start you on a cholesterol-lowering diet before giving you OMEGA-3-ACID ETHYL ESTERS CAPSULES, USP. Stay on this diet while taking OMEGA-3-ACID ETHYL ESTERS CAPSULES, USP.
- Your healthcare provider should do blood tests to check your triglyceride, bad cholesterol (LDL-C) and liver function (ALT and AST) levels while you take OMEGA-3-ACID ETHYL ESTERS CAPSULES, USP.

What are the possible side effects of OMEGA-3-ACID ETHYL ESTERS CAPSULES, USP?

OMEGA-3-ACID ETHYL ESTERS CAPSULES, USP may cause serious side effects, including:

- changes in certain blood tests.OMEGA-3-ACID ETHYL ESTERS CAPSULES, USP may cause an increase in the results of blood tests used to check your liver function and your bad cholesterol levels.
- increased risk of a heart rhythm problem in people who have a heart rhythm problem.OMEGA-3-ACID ETHYL ESTERS CAPSULES, USP may cause an increase in the frequency of a heart rhythm problem (atrial fibrillation or flutter), especially if the first few months of taking OMEGA-3-ACID ETHYL ESTERS CAPSULES, USP, if you already have a heart rhythm problem.

The most common side effects of OMEGA-3-ACID ETHYL ESTERS CAPSULES, USP include:

- burping
- upset stomach
- a change in your sense of taste

These are not all the possible side effects of OMEGA-3-ACID ETHYL ESTERS CAPSULES, USP.

Call your doctor for medical advice about side effects. You may report side effects to FDA at 1-800-FDA-1088.

How should I store OMEGA-3-ACID ETHYL ESTERS CAPSULES, USP?

- Store OMEGA-3-ACID ETHYL ESTERS CAPSULES, USP at room temperature between 68°F to 77°F (20°C to 25°C).
- Do not freeze OMEGA-3-ACID ETHYL ESTERS CAPSULES, USP.
- Safely throw away medicine that is out of date or no longer needed.

Keep OMEGA-3-ACID ETHYL ESTERS CAPSULES, USP and all medicines out of the reach of children.

General information about the safe and effective use of OMEGA-3-ACID ETHYL ESTERS CAPSULES, USP

Medicines are sometimes prescribed for purposes other than those listed in a Patient Information leaflet. Do not use OMEGA-3-ACID ETHYL ESTERS CAPSULES, USP for a condition for which it was not prescribed. Do not give OMEGA-3-ACID ETHYL ESTERS CAPSULES, USP to other people, even if they have the same symptoms you have. It may harm them.

You can ask your healthcare provider or pharmacist for information about OMEGA-3-ACID ETHYL ESTERS CAPSULES, USP that is written for health professionals.

What are the ingredients in OMEGA-3-ACID ETHYL ESTERS CAPSULES, USP?

Active Ingredient: omega-3-acid ethyl esters, mostly EPA and DHA

Inactive Ingredients: 4 mg alpha-tocopherol, gelatin, glycerin, hypromellose, propylene glycol, and titanium dioxide.

Manufactured By:
Patheon Softgels Inc.
High Point, NC 27265
USA

Manufactured For:
KD Pharma USA Inc.
12021 SW 144th Street
Miami, Florida 33186
USA

This patient labeling has been approved by the U.S. Food and Drug Administration.

Revised: November 2022
Revision: 1

Marketed by:

GSMS, Inc.

Camarillo, CA 93012 USA

PRINCIPAL DISPLAY PANEL - 120 Capsule Bottle Label

NDC 51407-763-12

Omega-3-Acid
Ethyl Esters
Capsules, USP

1 gram*

Swallow capsules whole.
Rx Only

120 Capsules